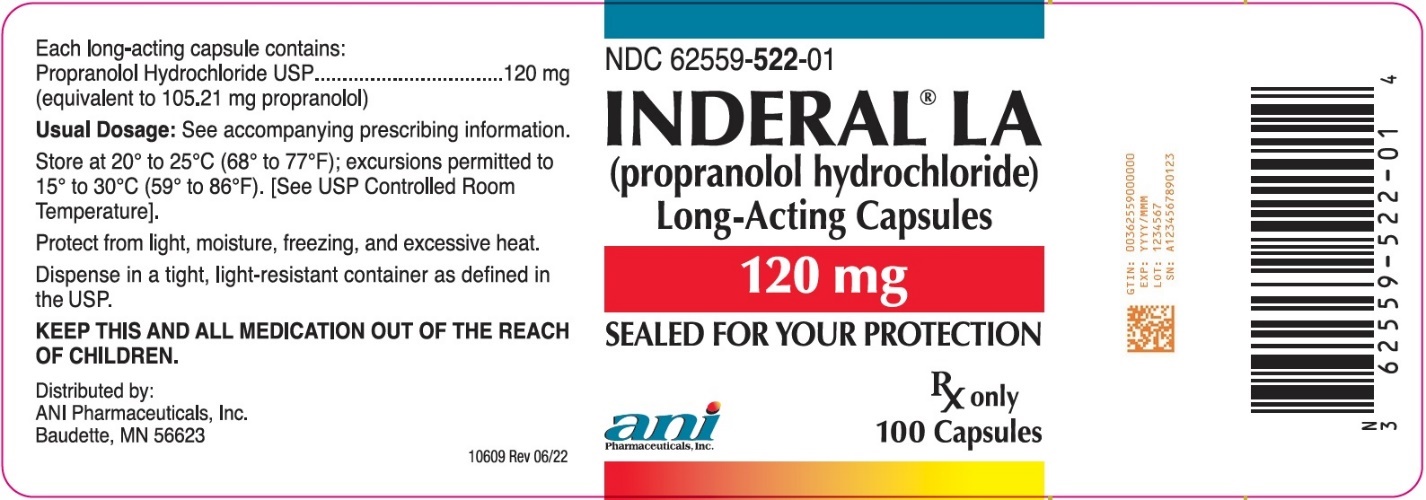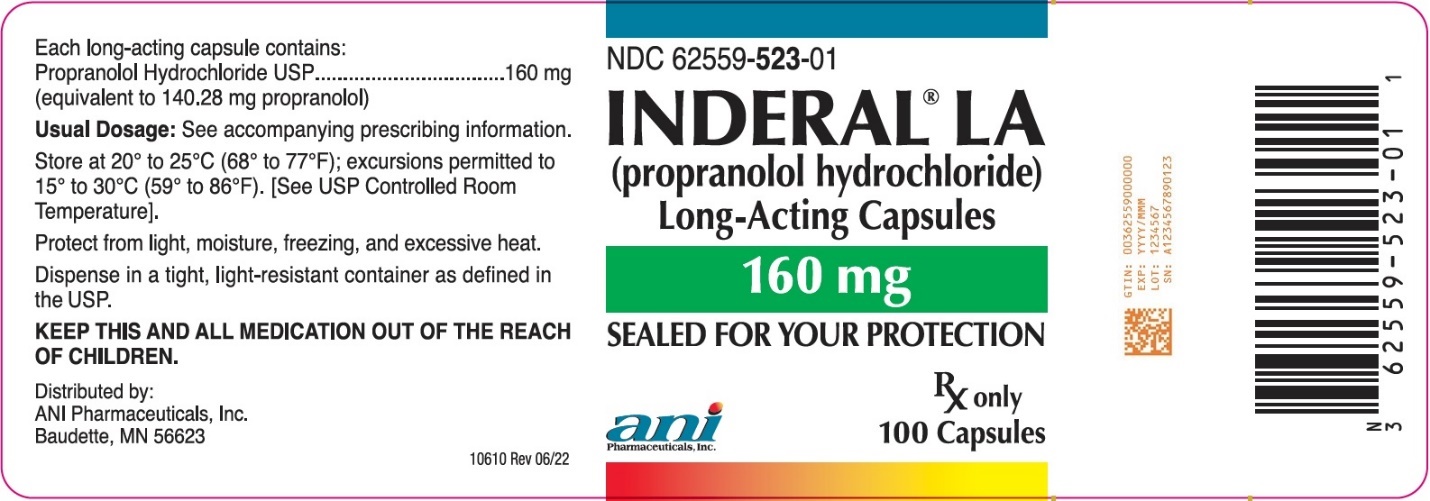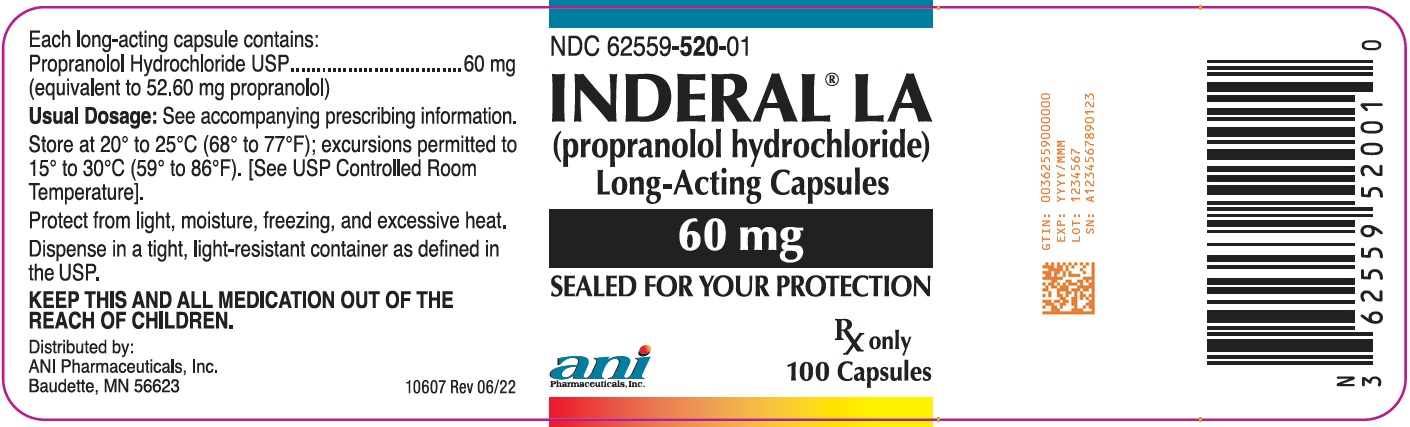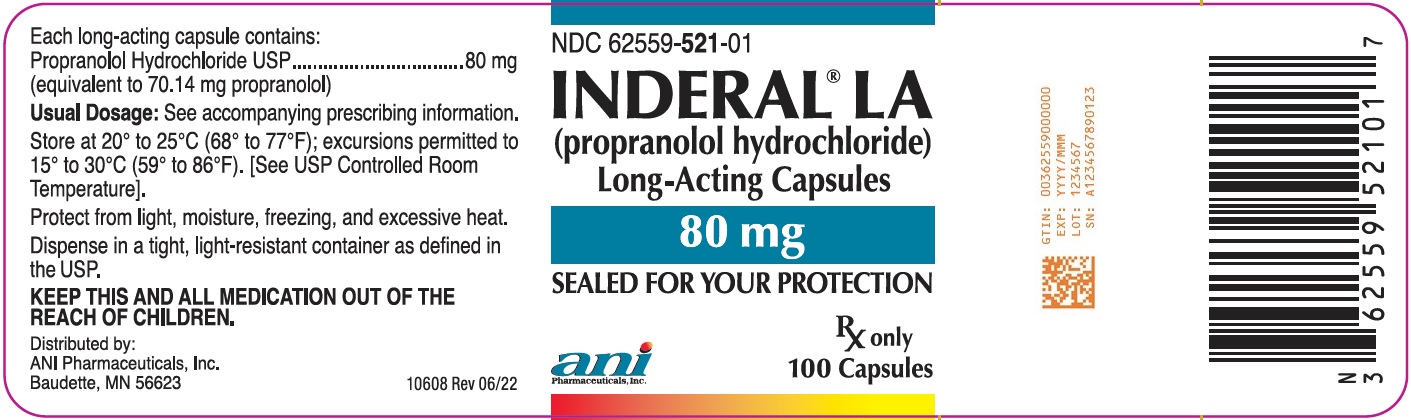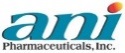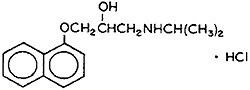 DRUG LABEL: INDERAL
NDC: 62559-520 | Form: CAPSULE, EXTENDED RELEASE
Manufacturer: ANI Pharmaceuticals, Inc.
Category: prescription | Type: HUMAN PRESCRIPTION DRUG LABEL
Date: 20240801

ACTIVE INGREDIENTS: PROPRANOLOL HYDROCHLORIDE 60 mg/1 1
INACTIVE INGREDIENTS: DIETHYL PHTHALATE; HYPROMELLOSE PHTHALATE (31% PHTHALATE, 40 CST); ETHYLCELLULOSE (10 MPA.S); POVIDONE K30; POLYETHYLENE GLYCOL 400; SUCROSE; STARCH, CORN; HYPROMELLOSE, UNSPECIFIED; POLYETHYLENE GLYCOL, UNSPECIFIED; GELATIN, UNSPECIFIED; TITANIUM DIOXIDE; D&C RED NO. 28; FD&C BLUE NO. 1

Inderal® LA
(propranolol hydrochloride)
Long-Acting Capsules

DESCRIPTION

Inderal® LA (propranolol hydrochloride) is a synthetic beta-adrenergic receptor-blocking agent chemically described as 2-Propanol, 1-[(1-methylethyl)amino]-3-(1-naphthalenyloxy)-, hydrochloride,(±)-. Its molecular and structural formulae are:

C16H21NO2 · HCl

Propranolol hydrochloride USP is a stable, white, crystalline solid which is readily soluble in water and ethanol. Its molecular weight is 295.80.

Inderal LA is formulated to provide a sustained release of propranolol hydrochloride USP. Inderal LA is available as 60 mg, 80 mg, 120 mg, and 160 mg capsules for oral administration.

- Each Inderal LA 60 mg capsule contains 60 mg propranolol hydrochloride USP (equivalent to 52.60 mg of propranolol).
- Each Inderal LA 80 mg capsule contains 80 mg propranolol hydrochloride USP (equivalent to 70.14 mg of propranolol).
- Each Inderal LA 120 mg capsule contains 120 mg propranolol hydrochloride USP (equivalent to 105.21 mg of propranolol).
- Each Inderal LA 160 mg capsule contains 160 mg propranolol hydrochloride USP (equivalent to 140.28 mg of propranolol).

The inactive ingredients contained in Inderal LA capsules are: diethyl phthalate, hypromellose phthalate, ethylcellulose, povidone, polyethylene glycol, corn starch, sucrose, hypromellose, gelatin capsules and titanium dioxide. In addition Inderal LA 60 mg capsules contain D&C Red No. 28 and FD&C Blue No. 1; Inderal LA 80 mg and 120 mg capsules contain FD&C Red No. 3 and FD&C Blue No. 1; Inderal LA 160 mg capsules contain FD&C Blue No. 1.

FDA approved dissolution specifications differ from USP.

CLINICAL PHARMACOLOGY

General

Propranolol is a nonselective, beta-adrenergic receptor-blocking agent possessing no other autonomic nervous system activity. It specifically competes with beta-adrenergic receptor-stimulating agents for available receptor sites. When access to beta-receptor sites is blocked by propranolol, the chronotropic, inotropic, and vasodilator responses to beta-adrenergic stimulation are decreased proportionately. At dosages greater than required for beta blockade, propranolol also exerts a quinidine-like or anesthetic-like membrane action, which affects the cardiac action potential. The significance of the membrane action in the treatment of arrhythmias is uncertain.

Inderal LA should not be considered a simple mg-for-mg substitute for conventional propranolol and the blood levels achieved do not match (are lower than) those of two to four times daily dosing with the same dose (see DOSAGE AND ADMINISTRATION). When changing to Inderal LA from conventional propranolol, a possible need for retitration upwards should be considered, especially to maintain effectiveness at the end of the dosing interval. In most clinical settings, however, such as hypertension or angina where there is little correlation between plasma levels and clinical effect, Inderal LA has been therapeutically equivalent to the same mg dose of conventional Inderal as assessed by 24-hour effects on blood pressure and on 24-hour exercise responses of heart rate, systolic pressure, and rate pressure product.

Mechanism of Action

The mechanism of the antihypertensive effect of propranolol has not been established. Among the factors that may be involved in contributing to the antihypertensive action include: (1) decreased cardiac output, (2) inhibition of renin release by the kidneys, and (3) diminution of tonic sympathetic nerve outflow from vasomotor centers in the brain. Although total peripheral resistance may increase initially, it readjusts to or below the pretreatment level with chronic use of propranolol. Effects of propranolol on plasma volume appear to be minor and somewhat variable.

In angina pectoris, propranolol generally reduces the oxygen requirement of the heart at any given level of effort by blocking the catecholamine-induced increases in the heart rate, systolic blood pressure, and the velocity and extent of myocardial contraction. Propranolol may increase oxygen requirements by increasing left ventricular fiber length, end diastolic pressure, and systolic ejection period. The net physiologic effect of beta-adrenergic blockade is usually advantageous and is manifested during exercise by delayed onset of pain and increased work capacity.

Propranolol exerts its antiarrhythmic effects in concentrations associated with beta-adrenergic blockade, and this appears to be its principal antiarrhythmic mechanism of action. In dosages greater than required for beta blockade, propranolol also exerts a quinidine-like or anesthetic-like membrane action which affects the cardiac action potential. The significance of the membrane action in the treatment of arrhythmias is uncertain.

The mechanism of the anti-migraine effect of propranolol has not been established. Beta-adrenergic receptors have been demonstrated in the pial vessels of the brain.

PHARMACOKINETICS AND DRUG METABOLISM

Absorption

Propranolol is highly lipophilic and almost completely absorbed after oral administration. However, it undergoes high first pass metabolism by the liver and on average, only about 25% of propranolol reaches the systemic circulation. Inderal LA Capsules (60, 80, 120, and 160 mg) release propranolol HCl at a controlled and predictable rate. Peak blood levels following dosing with Inderal LA occur at about 6 hours.

The effect of food on Inderal LA bioavailability has not been investigated.

Distribution

Approximately 90% of circulating propranolol is bound to plasma proteins (albumin and alpha-1-acid glycoprotein). The binding is enantiomer-selective. The S(-)-enantiomer is preferentially bound to alpha-1-glycoprotein and the R(+)-enantiomer preferentially bound to albumin. The volume of distribution of propranolol is approximately 4 liters/kg.

Propranolol crosses the blood-brain barrier and the placenta, and is distributed into breast milk.

Metabolism and Elimination

Propranolol is extensively metabolized with most metabolites appearing in the urine. Propranolol is metabolized through three primary routes: aromatic hydroxylation (mainly 4-hydroxylation), N-dealkylation followed by further side-chain oxidation, and direct glucuronidation. It has been estimated that the percentage contributions of these routes to total metabolism are 42%, 41% and 17%, respectively, but with considerable variability between individuals. The four major metabolites are propranolol glucuronide, naphthyloxylactic acid and glucuronic acid, and sulfate conjugates of 4-hydroxy propranolol.

In vitro studies have indicated that the aromatic hydroxylation of propranolol is catalyzed mainly by polymorphic CYP2D6. Side-chain oxidation is mediated mainly by CYP1A2 and to some extent by CYP2D6. 4-hydroxy propranolol is a weak inhibitor of CYP2D6.

Propranolol is also a substrate of CYP2C19 and a substrate for the intestinal efflux transporter, p-glycoprotein (p-gp). Studies suggest however that p-gp is not dose-limiting for intestinal absorption of propranolol in the usual therapeutic dose range.

In healthy subjects, no difference was observed between CYP2D6 extensive metabolizers (EMs) and poor metabolizers (PMs) with respect to oral clearance or elimination half-life. Partial clearance of 4-hydroxy propranolol was significantly higher and naphthyloxylactic acid was significantly lower in EMs than PMs.

When measured at steady state over a 24-hour period the areas under the propranolol plasma concentration-time curve (AUCs) for the Inderal LA capsules are approximately 60% to 65% of the AUCs for a comparable divided daily dose of Inderal Tablets. The lower AUCs for the Inderal LA capsules are due to greater hepatic metabolism of propranolol, resulting from the slower rate of absorption of propranolol. Over a twenty-four (24) hour period, blood levels are fairly constant for about twelve (12) hours, then decline exponentially. The apparent plasma half-life is about 10 hours.

Enantiomers

Propranolol is a racemic mixture of two enantiomers, R(+) and S(-). The S(-)-enantiomer is approximately 100 times as potent as the R(+)-enantiomer in blocking beta-adrenergic receptors. In normal subjects receiving oral doses of racemic propranolol, S(-)-enantiomer concentrations exceeded those of the R(+)-enantiomer by 40 to 90% as a result of stereoselective hepatic metabolism. Clearance of the pharmacologically active S(-)-propranolol is lower than R(+)-propranolol after intravenous and oral doses.

Special Population

Geriatric

The pharmacokinetics of Inderal LA have not been investigated in patients over 65 years of age.

In a study of 12 elderly (62 to 79 years old) and 12 young (25 to 33 years old) healthy subjects, the clearance of S-enantiomer of propranolol was decreased in the elderly. Additionally, the half-life of both the R- and S-propranolol were prolonged in the elderly compared with the young (11 hours vs. 5 hours).

Clearance of propranolol is reduced with aging due to decline in oxidation capacity (ring oxidation and side chain oxidation). Conjugation capacity remains unchanged. In a study of 32 patients age 30 to 84 years given a single 20-mg dose of propranolol, an inverse correlation was found between age and the partial metabolic clearances to 4-hydroxypropranolol (40HP ring oxidation) and to naphthoxylactic acid (NLA-side chain oxidation). No correlation was found between age and the partial metabolic clearance to propranolol glucuronide (PPLG conjugation).

Gender

In a study of 9 healthy women and 12 healthy men, neither the administration of testosterone nor the regular course of the menstrual cycle affected the plasma binding of the propranolol enantiomers. In contrast, there was a significant, although non-enantioselective diminution of the binding of propranolol after treatment with ethinyl estradiol. These findings are inconsistent with another study, in which administration of testosterone cypionate confirmed the stimulatory role of this hormone on propranolol metabolism and concluded that the clearance of propranolol in men is dependent on circulating concentrations of testosterone. In women, none of the metabolic clearances for propranolol showed any significant association with either estradiol or testosterone.

Race

A study conducted in 12 Caucasian and 13 African-American male subjects taking propranolol, showed that at steady state, the clearance of R(+)- and S(-)-propranolol were about 76% and 53% higher in African-Americans than in Caucasians, respectively.

Chinese subjects had a greater proportion (18% to 45% higher) of unbound propranolol in plasma compared to Caucasians, which was associated with a lower plasma concentration of alpha-1-acid glycoprotein.

Renal Insufficiency

The pharmacokinetics of Inderal LA have not been investigated in patients with renal insufficiency.

In a study conducted in 5 patients with chronic renal failure, 6 patients on regular dialysis, and 5 healthy subjects, who received a single oral dose of 40 mg of propranolol, the peak plasma concentrations (Cmax) of propranolol in the chronic renal failure group were 2 to 3-fold higher (161±41 ng/mL) than those observed in the dialysis patients (47±9 ng/mL) and in the healthy subjects (26±1 ng/mL). Propranolol plasma clearance was also reduced in the patients with chronic renal failure.

Studies have reported a delayed absorption rate and a reduced half-life of propranolol in patients with renal failure of varying severity. Despite this shorter plasma half-life, propranolol peak plasma levels were 3 to 4 times higher and total plasma levels of metabolites were up to 3 times higher in these patients than in subjects with normal renal function.

Chronic renal failure has been associated with a decrease in drug metabolism via down regulation of hepatic cytochrome P450 activity resulting in a lower "first-pass" clearance.

Propranolol is not significantly dialyzable.

Hepatic Insufficiency

The pharmacokinetics of Inderal LA have not been investigated in patients with hepatic insufficiency.

Propranolol is extensively metabolized by the liver. In a study conducted in 6 patients with cirrhosis and 7 healthy subjects receiving 160 mg of a long-acting preparation of propranolol once a day for 7 days, the steady-state propranolol concentration in patients with cirrhosis was increased 2.5-fold in comparison to controls. In the patients with cirrhosis, the half-life obtained after a single intravenous dose of 10 mg propranolol increased to 7.2 hours compared to 2.9 hours in control (see PRECAUTIONS).

Drug Interactions

All drug interaction studies were conducted with propranolol. There are no data on drug interactions with Inderal LA capsules.

Interactions with Substrates, Inhibitors or Inducers of Cytochrome P-450 Enzymes

Because propranolol's metabolism involves multiple pathways in the Cytochrome P-450 system (CYP2D6, 1A2, 2C19), co-administration with drugs that are metabolized by, or affect the activity (induction or inhibition) of one or more of these pathways may lead to clinically relevant drug interactions (see Drug Interactions under PRECAUTIONS).

Substrates or Inhibitors of CYP2D6

Blood levels and/or toxicity of propranolol may be increased by co-administration with substrates or inhibitors of CYP2D6, such as amiodarone, cimetidine, delavudin, fluoxetine, paroxetine, quinidine, and ritonavir. No interactions were observed with either ranitidine or lansoprazole.

Substrates or Inhibitors of CYP1A2

Blood levels and/or toxicity of propranolol may be increased by co-administration with substrates or inhibitors of CYP1A2, such as imipramine, cimetidine, ciprofloxacin, fluvoxamine, isoniazid, ritonavir, theophylline, zileuton, zolmitriptan, and rizatriptan.

Substrates or Inhibitors of CYP2C19

Blood levels and/or toxicity of propranolol may be increased by co-administration with substrates or inhibitors of CYP2C19, such as fluconazole, cimetidine, fluoxetine, fluvoxamine, tenioposide, and tolbutamide. No interaction was observed with omeprazole.

Inducers of Hepatic Drug Metabolism

Blood levels of propranolol may be decreased by co-administration with inducers such as rifampin, ethanol, phenytoin, and phenobarbital. Cigarette smoking also induces hepatic metabolism and has been shown to increase up to 77% the clearance of propranolol, resulting in decreased plasma concentrations.

Cardiovascular Drugs

Antiarrhythmics

The AUC of propafenone is increased by more than 200% by co-administration of propranolol.

The metabolism of propranolol is reduced by co-administration of quinidine, leading to a two to three fold increased blood concentration and greater degrees of clinical beta-blockade.

The metabolism of lidocaine is inhibited by co-administration of propranolol, resulting in a 25% increase in lidocaine concentrations.

Calcium Channel Blockers

The mean Cmax and AUC of propranolol are increased respectively, by 50% and 30% by co-administration of nisoldipine and by 80% and 47%, by co-administration of nicardipine.

The mean Cmax and AUC of nifedipine are increased by 64% and 79%, respectively, by co-administration of propranolol.

Propranolol does not affect the pharmacokinetics of verapamil and norverapamil. Verapamil does not affect the pharmacokinetics of propranolol.

Non-Cardiovascular Drugs

Migraine Drugs

Administration of zolmitriptan or rizatriptan with propranolol resulted in increased concentrations of zolmitriptan (AUC increased by 56% and Cmax by 37%) or rizatriptan (the AUC and Cmax were increased by 67% and 75%, respectively).

Theophylline

Co-administration of theophylline with propranolol decreases theophylline oral clearance by 30% to 52%.

Benzodiazepines

Propranolol can inhibit the metabolism of diazepam, resulting in increased concentrations of diazepam and its metabolites. Diazepam does not alter the pharmacokinetics of propranolol.

The pharmacokinetics of oxazepam, triazolam, lorazepam, and alprazolam are not affected by co-administration of propranolol.

Neuroleptic Drugs

Co-administration of long-acting propranolol at doses greater than or equal to 160 mg/day resulted in increased thioridazine plasma concentrations ranging from 55% to 369% and increased thioridazine metabolite (mesoridazine) concentrations ranging from 33% to 209%.

Co-administration of chlorpromazine with propranolol resulted in a 70% increase in propranolol plasma level.

Anti-Ulcer Drugs

Co-administration of propranolol with cimetidine, a non-specific CYP450 inhibitor, increased propranolol AUC and Cmax by 46% and 35%, respectively. Co-administration with aluminum hydroxide gel (1200 mg) may result in a decrease in propranolol concentrations.

Co-administration of metoclopramide with the long-acting propranolol did not have a significant effect on propranolol's pharmacokinetics.

Lipid Lowering Drugs

Co-administration of cholestyramine or colestipol with propranolol resulted in up to 50% decrease in propranolol concentrations.

Co-administration of propranolol with lovastatin or pravastatin, decreased 18% to 23% the AUC of both, but did not alter their pharmacodynamics. Propranolol did not have an effect on the pharmacokinetics of fluvastatin.

Warfarin

Concomitant administration of propranolol and warfarin has been shown to increase warfarin bioavailability and increase prothrombin time.

PHARMACODYNAMICS AND CLINICAL EFFECTS

Hypertension

In a retrospective, uncontrolled study, 107 patients with diastolic blood pressure 110 to 150 mmHg received propranolol 120 mg t.i.d. for at least 6 months, in addition to diuretics and potassium, but with no other hypertensive agent. Propranolol contributed to control of diastolic blood pressure, but the magnitude of the effect of propranolol on blood pressure cannot be ascertained.

Four double-blind, randomized, crossover studies were conducted in a total of 74 patients with mild or moderately severe hypertension treated with Inderal LA 160 mg once daily or propranolol 160 mg given either once daily or in two 80 mg doses. Three of these studies were conducted over a 4-week treatment period. One study was assessed after a 24-hour period. Inderal LA was as effective as propranolol in controlling hypertension (pulse rate, systolic and diastolic blood pressure) in each of these trials.

Angina Pectoris

In a double-blind, placebo-controlled study of 32 patients of both sexes, aged 32 to 69 years, with stable angina, propranolol 100 mg t.i.d. was administered for 4 weeks and shown to be more effective than placebo in reducing the rate of angina episodes and in prolonging total exercise time.

Twelve male patients with moderately severe angina pectoris were studied in a double-blind, crossover study. Patients were randomized to either Inderal LA 160 mg daily or conventional propranolol 40 mg four times a day for 2 weeks. Nitroglycerine tablets were allowed during the study. Blood pressure, heart rate and ECG's were recorded during serial exercise treadmill testing. Inderal LA was as effective as conventional propranolol for exercise heart rate, systolic and diastolic blood pressure, duration of anginal pain and ST-segment depression before or after exercise, exercise duration, angina attack rate and nitroglycerine consumption.

In another double-blind, randomized, crossover trial, the effectiveness of Inderal LA 160 mg daily and conventional propranolol 40 mg four times a day were evaluated in 13 patients with angina. ECG's were recorded while patients exercised until angina developed. Inderal LA was as effective as conventional propranolol for amount of exercise performed, ST-segment depression, number of anginal attacks, amount of nitroglycerine consumed, systolic and diastolic blood pressures and heart rate at rest and after exercise.

Migraine

In a 34-week, placebo-controlled, 4-period, dose-finding crossover study with a double-blind randomized treatment sequence, 62 patients with migraine received propranolol 20 to 80 mg 3 or 4 times daily. The headache unit index, a composite of the number of days with headache and the associated severity of the headache, was significantly reduced for patients receiving propranolol as compared to those on placebo.

Hypertrophic Subaortic Stenosis

In an uncontrolled series of 13 patients with New York Heart Association (NYHA) class 2 or 3 symptoms and hypertrophic subaortic stenosis diagnosed at cardiac catheterization, oral propranolol 40 to 80 mg t.i.d. was administered and patients were followed for up to 17 months. Propranolol was associated with improved NYHA class for most patients.

INDICATIONS AND USAGE

Hypertension

Inderal LA is indicated in the management of hypertension. It may be used alone or used in combination with other antihypertensive agents, particularly a thiazide diuretic. Inderal LA is not indicated in the management of hypertensive emergencies.

Angina Pectoris Due to Coronary Atherosclerosis

Inderal LA is indicated to decrease angina frequency and increase exercise tolerance in patients with angina pectoris.

Migraine

Inderal LA is indicated for the prophylaxis of common migraine headache. The efficacy of propranolol in the treatment of a migraine attack that has started has not been established, and propranolol is not indicated for such use.

Hypertrophic Subaortic Stenosis

Inderal LA improves NYHA functional class in symptomatic patients with hypertrophic subaortic stenosis.

CONTRAINDICATIONS

Propranolol is contraindicated in 1) cardiogenic shock; 2) sinus bradycardia and greater than first-degree block; 3) bronchial asthma; and 4) in patients with known hypersensitivity to propranolol hydrochloride.

WARNINGS

Angina Pectoris

There have been reports of exacerbation of angina and, in some cases, myocardial infarction, following abrupt discontinuance of propranolol therapy. Therefore, when discontinuance of propranolol is planned, the dosage should be gradually reduced over at least a few weeks, and the patient should be cautioned against interruption or cessation of therapy without the physician's advice. If propranolol therapy is interrupted and exacerbation of angina occurs, it usually is advisable to reinstitute propranolol therapy and take other measures appropriate for the management of unstable angina pectoris. Since coronary artery disease may be unrecognized, it may be prudent to follow the above advice in patients considered at risk of having occult atherosclerotic heart disease who are given propranolol for other indications.

Hypersensitivity and Skin Reactions

Hypersensitivity reactions, including anaphylactic/anaphylactoid reactions, have been associated with the administration of propranolol (see ADVERSE REACTIONS).

Cutaneous reactions, including Stevens-Johnson Syndrome, toxic epidermal necrolysis, exfoliative dermatitis, erythema multiforme, and urticaria, have been reported with use of propranolol (see ADVERSE REACTIONS).

Cardiac Failure

Sympathetic stimulation may be a vital component supporting circulatory function in patients with congestive heart failure, and its inhibition by beta blockade may precipitate more severe failure. Although beta-blockers should be avoided in overt congestive heart failure, some have been shown to be highly beneficial when used with close follow-up in patients with a history of failure who are well compensated and are receiving diuretics as needed. Beta-adrenergic blocking agents do not abolish the inotropic action of digitalis on heart muscle.

In Patients without a History of Heart Failure, continued use of beta-blockers can, in some cases, lead to cardiac failure.

Nonallergic Bronchospasm (e.g., Chronic Bronchitis, Emphysema)

In general, patients with bronchospastic lung disease should not receive beta-blockers. Propranolol should be administered with caution in this setting since it may provoke a bronchial asthmatic attack by blocking bronchodilation produced by endogenous and exogenous catecholamine stimulation of beta-receptors.

Major Surgery

Chronically administered beta-blocking therapy should not be routinely withdrawn prior to major surgery, however the impaired ability of the heart to respond to reflex adrenergic stimuli may augment the risks of general anesthesia and surgical procedures.

Hypoglycemia

Beta-blockers may prevent early warning signs of hypoglycemia, such as tachycardia, and increase the risk for severe or prolonged hypoglycemia at any time during treatment, especially in patients with diabetes mellitus or children and patients who are fasting (i.e., surgery, not eating regularly, or are vomiting). If severe hypoglycemia occurs, patients should be instructed to seek emergency treatment.

Hypoglycemia has been reported in patients taking propranolol after prolonged physical exertion and in patients with renal insufficiency.

Thyrotoxicosis

Beta-adrenergic blockade may mask certain clinical signs of hyperthyroidism. Therefore, abrupt withdrawal of propranolol may be followed by an exacerbation of symptoms of hyperthyroidism, including thyroid storm. Propranolol may change thyroid-function tests, increasing T4 and reverse T3, and decreasing T3.

Wolff-Parkinson-White Syndrome

Beta-adrenergic blockade in patients with Wolff-Parkinson-White syndrome and tachycardia has been associated with severe bradycardia requiring treatment with a pacemaker. In one case, this result was reported after an initial dose of 5 mg propranolol.

PRECAUTIONS

General

Propranolol should be used with caution in patients with impaired hepatic or renal function. Inderal LA is not indicated for the treatment of hypertensive emergencies.

Beta-adrenergic receptor blockade can cause reduction of intraocular pressure. Patients should be told that Inderal LA may interfere with the glaucoma screening test. Withdrawal may lead to a return of increased intraocular pressure.

While taking beta-blockers, patients with a history of severe anaphylactic reaction to a variety of allergens may be more reactive to repeated challenge, either accidental, diagnostic, or therapeutic. Such patients may be unresponsive to the usual doses of epinephrine used to treat allergic reaction.

Information for Patients

Inform patients or caregivers that there is a risk of hypoglycemia when Inderal LA is given to patients who are fasting or who are vomiting. Monitor for symptoms of hypoglycemia.

Clinical Laboratory Tests

In patients with hypertension, use of propranolol has been associated with elevated levels of serum potassium, serum transaminases, and alkaline phosphatase. In severe heart failure, the use of propranolol has been associated with increases in Blood Urea Nitrogen.

Drug Interactions

Caution should be exercised when Inderal LA is administered with drugs that have an affect on CYP2D6, 1A2, or 2C19 metabolic pathways. Co-administration of such drugs with propranolol may lead to clinically relevant drug interactions and changes on its efficacy and/or toxicity (see Drug Interactions in PHARMACOKINETICS AND DRUG METABOLISM).

Alcohol when used concomitantly with propranolol, may increase plasma levels of propranolol.

Cardiovascular Drugs

Antiarrhythmics

Propafenone has negative inotropic and beta-blocking properties that can be additive to those of propranolol.

Quinidine increases the concentration of propranolol and produces greater degrees of clinical beta-blockade and may cause postural hypotension.

Amiodarone is an antiarrhythmic agent with negative chronotropic properties that may be additive to those seen with β-blockers such as propranolol.

The clearance of lidocaine is reduced with administration of propranolol. Lidocaine toxicity has been reported following co-administration with propranolol.

Caution should be exercised when administering Inderal LA with drugs that slow A-V nodal conduction, e.g., lidocaine and calcium channel blockers.

Digitalis Glycosides

Both digitalis glycosides and beta-blockers slow atrioventricular conduction and decrease heart rate. Concomitant use can increase the risk of bradycardia.

Calcium Channel Blockers

Caution should be exercised when patients receiving a beta-blocker are administered a calcium-channel-blocking drug with negative inotropic and/or chronotropic effects. Both agents may depress myocardial contractility or atrioventricular conduction.

There have been reports of significant bradycardia, heart failure, and cardiovascular collapse with concurrent use of verapamil and beta-blockers.

Co-administration of propranolol and diltiazem in patients with cardiac disease has been associated with bradycardia, hypotension, high degree heart block, and heart failure.

ACE Inhibitors

When combined with beta-blockers, ACE inhibitors can cause hypotension, particularly in the setting of acute myocardial infarction.

The antihypertensive effects of clonidine may be antagonized by beta-blockers. Inderal LA should be administered cautiously to patients withdrawing from clonidine.

Alpha Blockers

Prazosin has been associated with prolongation of first dose hypotension in the presence of beta-blockers.

Postural hypotension has been reported in patients taking both beta-blockers and terazosin or doxazosin.

Reserpine

Patients receiving catecholamine-depleting drugs, such as reserpine should be closely observed for excessive reduction of resting sympathetic nervous activity, which may result in hypotension, marked bradycardia, vertigo, syncopal attacks, or orthostatic hypotension.

Inotropic Agents

Patients on long-term therapy with propranolol may experience uncontrolled hypertension if administered epinephrine as a consequence of unopposed alpha-receptor stimulation. Epinephrine is therefore not indicated in the treatment of propranolol overdose (see OVERDOSAGE).

Isoproterenol and Dobutamine

Propranolol is a competitive inhibitor of beta-receptor agonists, and its effects can be reversed by administration of such agents, e.g., dobutamine or isoproterenol. Also, propranolol may reduce sensitivity to dobutamine stress echocardiography in patients undergoing evaluation for myocardial ischemia.

Non-Cardiovascular Drugs

Nonsteroidal Anti-Inflammatory Drugs

Nonsteroidal anti-inflammatory drugs (NSAIDs) have been reported to blunt the antihypertensive effect of beta-adrenoreceptor blocking agents.

Administration of indomethacin with propranolol may reduce the efficacy of propranolol in reducing blood pressure and heart rate.

Antidepressants

The hypotensive effects of MAO inhibitors or tricyclic antidepressants may be exacerbated when administered with beta-blockers by interfering with the beta-blocking activity of propranolol.

Anesthetic Agents

Methoxyflurane and trichloroethylene may depress myocardial contractility when administered with propranolol.

Warfarin

Propranolol when administered with warfarin increases the concentration of warfarin. Prothrombin time, therefore, should be monitored.

Neuroleptic Drugs

Hypotension and cardiac arrest have been reported with the concomitant use of propranolol and haloperidol.

Thyroxine

Thyroxine may result in a lower than expected T3 concentration when used concomitantly with propranolol.

Carcinogenesis, Mutagenesis, Impairment of Fertility

In dietary administration studies in which mice and rats were treated with propranolol hydrochloride for up to 18 months at doses of up to 150 mg/kg/day, there was no evidence of drug-related tumorigenesis. On a body surface area basis, this dose in the mouse and rat is, respectively, about equal to and about twice the maximum recommended human oral daily dose (MRHD) of 640 mg propranolol hydrochloride. In a study in which both male and female rats were exposed to propranolol hydrochloride in their diets at concentrations of up to 0.05% (about 50 mg/kg body weight and less than the MRHD), from 60 days prior to mating and throughout pregnancy and lactation for two generations, there were no effects on fertility. Based on differing results from Ames Tests performed by different laboratories, there is equivocal evidence for a genotoxic effect of propranolol in bacteria (S. typhimurium strain TA 1538).

Pregnancy

In a series of reproductive and developmental toxicology studies, propranolol was given to rats by gavage or in the diet throughout pregnancy and lactation. At doses of 150 mg/kg/day, but not at doses of 80 mg/kg/day (equivalent to the MRHD on a body surface area basis), treatment was associated with embryotoxicity (reduced litter size and increased resorption rates) as well as neonatal toxicity (deaths). Propranolol hydrochloride also was administered (in the feed) to rabbits (throughout pregnancy and lactation) at doses as high as 150 mg/kg/day (about 5 times the maximum recommended human oral daily dose). No evidence of embryo or neonatal toxicity was noted.

There are no adequate and well-controlled studies in pregnant women. Intrauterine growth retardation, small placentas, and congenital abnormalities have been reported in neonates whose mothers received propranolol during pregnancy. Neonates whose mothers are receiving propranolol at parturition have exhibited bradycardia, hypoglycemia and/or respiratory depression. Adequate facilities for monitoring such infants at birth should be available. Inderal LA should be used during pregnancy only if the potential benefit justifies the potential risk to the fetus.

Nursing Mothers

Propranolol is excreted in human milk. Caution should be exercised when Inderal LA is administered to a nursing woman.

Pediatric Use

Safety and effectiveness of propranolol in pediatric patients have not been established.

Bronchospasm and congestive heart failure have been reported coincident with the administration of propranolol therapy in pediatric patients.

Geriatric Use

Clinical studies of Inderal LA did not include sufficient numbers of subjects aged 65 and over to determine whether they respond differently from younger subjects. Other reported clinical experience has not identified differences in responses between the elderly and younger patients. In general, dose selection for an elderly patient should be cautious, usually starting at the low end of the dosing range, reflecting the greater frequency of the decreased hepatic, renal or cardiac function, and of concomitant disease or other drug therapy.

ADVERSE REACTIONS

The following adverse events were observed and have been reported in patients using propranolol.

Cardiovascular: Bradycardia; congestive heart failure; intensification of AV block; hypotension; paresthesia of hands; thrombocytopenic purpura; arterial insufficiency, usually of the Raynaud type.

Central Nervous System: Light-headedness; mental depression manifested by insomnia, lassitude, weakness, fatigue; catatonia; visual disturbances; hallucinations; vivid dreams; an acute reversible syndrome characterized by disorientation for time and place, short-term memory loss, emotional lability, slightly clouded sensorium, and decreased performance on neuropsychometrics. For immediate release formulations, fatigue, lethargy, and vivid dreams appear dose related.

Gastrointestinal: Nausea, vomiting, epigastric distress, abdominal cramping, diarrhea, constipation, mesenteric arterial thrombosis, ischemic colitis.

Allergic: Hypersensitivity reactions, including anaphylactic/anaphylactoid reactions; pharyngitis and agranulocytosis; erythematous rash; fever combined with aching and sore throat; laryngospasm; respiratory distress.

Respiratory: Bronchospasm.

Hematologic: Agranulocytosis, nonthrombocytopenic purpura, and thrombocytopenic purpura.

Autoimmune: Systemic lupus erythematosus (SLE).

Skin and Mucous Membranes: Stevens-Johnson Syndrome, toxic epidermal necrolysis, dry eyes, exfoliative dermatitis, erythema multiforme, urticaria, alopecia, SLE-like reactions, and psoriasisiform rashes. Oculomucocutaneous syndrome involving the skin, serous membranes, and conjunctivae reported for a beta-blocker (practolol) have not been associated with propranolol.

Genitourinary: Male impotence; Peyronie's disease.

OVERDOSAGE

Propranolol is not significantly dialyzable. In the event of overdosage or exaggerated response, the following measures should be employed:

General: If ingestion is or may have been recent, evacuate gastric contents, taking care to prevent pulmonary aspiration.

Supportive Therapy: Hypotension and bradycardia have been reported following propranolol overdose and should be treated appropriately. Glucagon can exert potent inotropic and chronotropic effects and may be particularly useful for the treatment of hypotension or depressed myocardial function after a propranolol overdose. Glucagon should be administered as 50 to 150 mcg/kg intravenously followed by continuous drip of 1 to 5 mg/hour for positive chronotropic effect. Isoproterenol, dopamine or phosphodiesterase inhibitors may also be useful. Epinephrine, however, may provoke uncontrolled hypertension. Bradycardia can be treated with atropine or isoproterenol. Serious bradycardia may require temporary cardiac pacing.

The electrocardiogram, pulse, blood pressure, neurobehavioral status and intake and output balance must be monitored. Isoproterenol and aminophylline may be used for bronchospasm.

DOSAGE AND ADMINISTRATION

General

Inderal LA provides propranolol hydrochloride in a sustained-release capsule for administration once daily. If patients are switched from Inderal Tablets to Inderal LA Capsules, care should be taken to assure that the desired therapeutic effect is maintained. Inderal LA should not be considered a simple mg-for-mg substitute for Inderal. Inderal LA has different kinetics and produces lower blood levels. Retitration may be necessary, especially to maintain effectiveness at the end of the 24-hour dosing interval.

Hypertension

The usual initial dosage is 80 mg Inderal LA once daily, whether used alone or added to a diuretic. The dosage may be increased to 120 mg once daily or higher until adequate blood pressure control is achieved. The usual maintenance dosage is 120 to 160 mg once daily. In some instances a dosage of 640 mg may be required. The time needed for full hypertensive response to a given dosage is variable and may range from a few days to several weeks.

Angina Pectoris

Starting with 80 mg Inderal LA once daily, dosage should be gradually increased at three- to seven-day intervals until optimal response is obtained. Although individual patients may respond at any dosage level, the average optimal dosage appears to be 160 mg once daily. In angina pectoris, the value and safety of dosage exceeding 320 mg per day have not been established.

If treatment is to be discontinued, reduce dosage gradually over a period of a few weeks (see "WARNINGS").

Migraine

The initial oral dose is 80 mg Inderal LA once daily. The usual effective dose range is 160 to 240 mg once daily. The dosage may be increased gradually to achieve optimal migraine prophylaxis. If a satisfactory response is not obtained within four to six weeks after reaching the maximal dose, Inderal LA therapy should be discontinued. It may be advisable to withdraw the drug gradually over a period of several weeks depending on the patient's age, comorbidity, and dose of Inderal LA.

Hypertrophic Subaortic Stenosis

The usual dosage is 80 to 160 mg Inderal LA once daily.

HOW SUPPLIED

Inderal® LA (propranolol hydrochloride) Long-Acting Capsules

Each white/light-blue capsule, imprinted with three rings and reverse imprinted ‘INDERAL LA 60’, contains 60 mg of propranolol hydrochloride USP (equivalent to 52.60 mg of propranolol) and are available in:
Bottles of 30 NDC 62559-520-30
Bottles of 100 NDC 62559-520-01

Each light-blue capsule, imprinted with three rings and reverse imprinted ‘INDERAL LA 80’, contains 80 mg of propranolol hydrochloride USP (equivalent to 70.14 mg of propranolol) and are available in:
Bottles of 30 NDC 62559-521-30
Bottles of 100 NDC 62559-521-01

Each light-blue/dark-blue capsule, imprinted with three rings and reverse imprinted ‘INDERAL LA 120’, contains 120 mg of propranolol hydrochloride USP (equivalent to 105.21 mg of propranolol) and are available in:
Bottles of 30 NDC 62559-522-30
Bottles of 100 NDC 62559-522-01

Each dark-blue capsule, imprinted with three rings and reverse imprinted ‘INDERAL LA 160’, contains 160 mg of propranolol hydrochloride USP (equivalent to 140.28 mg of propranolol) and are available in:
Bottles of 30 NDC 62559-523-30
Bottles of 100 NDC 62559-523-01

Store at 20° to 25°C (68° to 77°F); excursions permitted to 15° to 30°C (59° to 86°F). [See USP Controlled Room Temperature]

Protect from light, moisture, freezing, and excessive heat.

Dispense in a tight, light-resistant container as defined in the USP.

For medical inquires, contact ANI Pharmaceuticals, Inc. at 1-800-308-6755.

Distributed by:
ANI Pharmaceuticals, Inc.
Baudette, MN 56623

10611 Rev 06/24

PRINCIPAL DISPLAY PANEL - 60 mg Capsule

NDC 62559-520-01
INDERAL® LA (propranolol hydrochloride) Long-Acting Capsules
60 mg
Rx only
100 Capsules

PRINCIPAL DISPLAY PANEL - 80 mg Capsule

NDC 62559-521-01
INDERAL® LA (propranolol hydrochloride) Long-Acting Capsules
80 mg
Rx only
100 Capsules

PRINCIPAL DISPLAY PANEL - 120 mg Capsule

NDC 62559-522-01
INDERAL® LA (propranolol hydrochloride) Long-Acting Capsules
120 mg
Rx only
100 Capsules

PRINCIPAL DISPLAY PANEL - 160 mg Capsule

NDC 62559-523-01
INDERAL® LA (propranolol hydrochloride) Long-Acting Capsules
160 mg
Rx only
100 Capsules